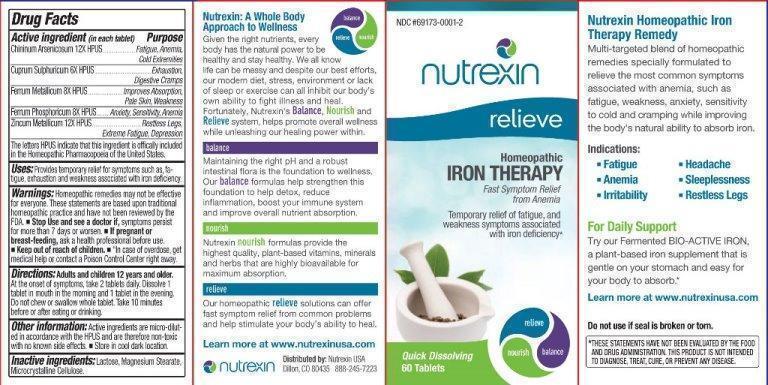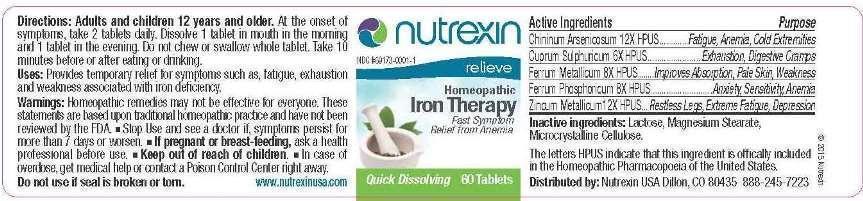 DRUG LABEL: Iron Therapy
NDC: 69173-0001 | Form: TABLET
Manufacturer: Nutrexin USA
Category: homeopathic | Type: HUMAN OTC DRUG LABEL
Date: 20191111

ACTIVE INGREDIENTS: QUININE ARSENATE 12 [hp_X]/1 1; CUPRIC SULFATE 6 [hp_X]/1 1; IRON 8 [hp_X]/1 1; FERROSOFERRIC PHOSPHATE 8 [hp_X]/1 1; ZINC 12 [hp_X]/1 1
INACTIVE INGREDIENTS: LACTOSE; MAGNESIUM STEARATE; CELLULOSE, MICROCRYSTALLINE

DRUG FACTS:

ACTIVE INGREDIENTS:

Chininum Arsenicosum 12X, Cuprum Sulphuricum 6X, Ferrum Metallicum 8X, Ferrum Phosphoricum 8X, Zincum Metallicum 12X

USES:

Provides temporary relief for symptoms such as, fatigue, exhaustion and weakness associated with iron deficiency.

WARNINGS:

Homeopathic remedies may not be effective for everyone. These statements are based upon traditional homeopathic practice and have not been reviewed by the FDA.

• Stop Use and see a doctor if, symptoms persist for more than 7 days or worsen.

• If pregnant or breast-feeding, ask a health professional before use.

• Keep out of reach of children.

• In case of overdose, get medical help or contact a Poison Control Center right away.

Do not use if seal is broken or torn.

*THESE STATMENTS HAVE NOT BEEN EVALUTAED BY THE FOOD AND DRUG ADMINISTRATION. THIS PRODUCT IS NOT INTENDED TO DIAGNOSE, TREAT, CURE OR PREVENT ANY DISEASE.

Keep out of reach of children. In case of overdose, get medical help or contact a Poison Control Center right away.

DIRECTIONS:

Adults and children 12 years and older. At the onset of symptoms, take 2 tablets daily. Dissolve 1 tablet in mouth in the morning and 1 tablet in the evening. Do not chew or swallow whole tablet. Take 10 minutes before or after eating or drinking.

USES:

Provides temporary relief for symptoms such as, fatigue, exhaustion and weakness associated with iron deficiency.

INACTIVE INGREDIENTS:

Lactose (Fast Flo Lactose USP 316), Magnesium Stearate, Microcrystalline Cellulose

QUESTIONS:

Distributed by:

Nutrexin USA

Dillon, CO 80435

888-245-7223

www.nutrexinusa.com

PACKAGE LABEL DISPLAY:

NDC #69173-0001-1

nutrexin

relieve

Homeopathic

Iron Therapy

Fast Symptom Relief from Anemia

Temporary relief of fatigue, and weakness symptoms associated with iron deficiency.*

Quick Dissolving 60 Tablets